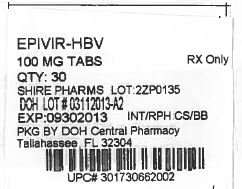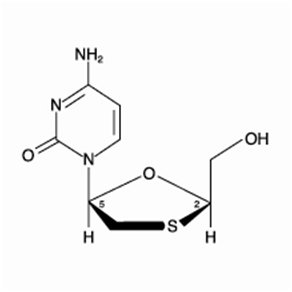 DRUG LABEL: EPIVIR
NDC: 53808-0893 | Form: TABLET, FILM COATED
Manufacturer: State of Florida DOH Central Pharmacy
Category: prescription | Type: HUMAN PRESCRIPTION DRUG LABEL
Date: 20140303

ACTIVE INGREDIENTS: LAMIVUDINE 100 mg/1 1
INACTIVE INGREDIENTS: HYPROMELLOSES; POLYETHYLENE GLYCOLS; MAGNESIUM STEARATE; CELLULOSE, MICROCRYSTALLINE; POLYSORBATE 80; FERRIC OXIDE RED; SODIUM STARCH GLYCOLATE TYPE A POTATO; TITANIUM DIOXIDE; FERRIC OXIDE YELLOW

HIGHLIGHTS OF PRESCRIBING INFORMATION

These highlights do not include all the information needed to use EPIVIR-HBV safely and effectively. See full prescribing information for EPIVIR-HBV.
EPIVIR-HBV (lamivudine) tablets for oral use
EPIVIR-HBV (lamivudine) oral solution
Initial U.S. Approval: 1995

WARNING: RISK OF LACTIC ACIDOSIS, EXACERBATIONS OF HEPATITIS B UPON DISCONTINUATION OF EPIVIR-HBV®, AND RISK OF HIV-1 RESISTANCE IF EPIVIR-HBV IS USED IN PATIENTS WITH UNRECOGNIZED OR UNTREATED HIV-1.

See full prescribing information for complete boxed warning.

- Lactic acidosis and severe hepatomegaly with steatosis, including fatal cases, have been reported with the use of nucleoside analogues. Suspend treatment if clinical or laboratory findings suggestive of lactic acidosis or pronounced hepatotoxicity occur. (5.1)
- Severe acute exacerbations of hepatitis B have been reported in patients who have discontinued anti-hepatitis B therapy (including EPIVIR-HBV). Monitor hepatic function closely in these patients and, if appropriate, initiate anti-hepatitis B treatment. (5.2)
- EPIVIR‑HBV tablets and oral solution contain a lower dose of the same active ingredient (lamivudine) as EPIVIR tablets and oral Solution used to treat HIV-1 infection. HIV-1 resistance may emerge in chronic hepatitis B patients with unrecognized or untreated HIV-1 infection because the lamivudine dosage in EPIVIR‑HBV is subtherapeutic and monotherapy is inappropriate for the treatment of HIV-1 infection. HIV counseling and testing should be offered to all patients before beginning treatment with EPIVIR‑HBV and periodically during treatment. (5.3)

1 INDICATIONS AND USAGE

- EPIVIR-HBV is a nucleoside analogue reverse transcriptase inhibitor indicated for the treatment of chronic hepatitis B virus infection associated with evidence of hepatitis B viral replication and active liver inflammation. (1)

DOSAGE AND ADMINISTRATION

- Adult patients: 100 mg, once daily. (2.2)
- Pediatric patients aged 2 to 17 years: 3 mg per kg once daily up to 100 mg once daily. Prescribe oral solution for pediatric patients requiring less than 100 mg daily. (2.3)
- Patients with renal impairment: Doses of EPIVIR-HBV must be adjusted in accordance with renal function. (2.4)
- EPIVIR-HBV should not be used with other medications that contain lamivudine or emtricitabine. (2.5)

3 DOSAGE FORMS AND STRENGTHS

- Tablets: 100 mg (3)
- Oral Solution: 5 mg per mL (3)

4 CONTRAINDICATIONS

Patients with previously demonstrated clinically significant hypersensitivity (e.g., anaphylaxis) to any of the components of the products. (4)

WARNINGS AND PRECAUTIONS

- EPIVIR-HBV should not be used with other medications that contain lamivudine or with medications that contain emtricitabine. (5.4)
- Emergence of Resistance-Associated HBV Substitutions: Monitor ALT and HBV DNA levels during lamivudine treatment to aid in treatment decisions if emergence of viral mutants or loss of therapeutic response is suspected. (2.6, 5.5)

6 ADVERSE REACTIONS

- The most common reported adverse reactions in those receiving EPIVIR-HBV (incidence greater than or equal to 10% and reported at a rate greater than placebo) were ear, nose and throat infections, sore throat, and diarrhea. (6.1)

To report SUSPECTED ADVERSE REACTIONS, contact GlaxoSmithKline at 1-888-825-5249 at 1-877-844-8872 or FDA at 1-800-FDA-1088 or www.fda.gov/medwatch.

FULL PRESCRIBING INFORMATION

WARNING: RISK OF LACTIC ACIDOSIS, EXACERBATIONS OF HEPATITIS B UPON DISCONTINUATION OF EPIVIR-HBV®, AND RISK OF HIV-1 RESISTANCE IF EPIVIR-HBV IS USED IN PATIENTS WITH UNRECOGNIZED OR UNTREATED HIV-1.

Lactic Acidosis and Severe Hepatomegaly: Lactic acidosis and severe hepatomegaly with steatosis, including fatal cases, have been reported with the use of nucleoside analogues alone or in combination, including EPIVIR-HBV. Suspend treatment if clinical or laboratory findings suggestive of lactic acidosis or pronounced hepatotoxicity occur [see Warnings and Precautions (5.1)].

Exacerbations of Hepatitis B Upon Discontinuation of EPIVIR-HBV: Severe acute exacerbations of hepatitis B have been reported in patients who have discontinued anti-hepatitis B therapy (including EPIVIR-HBV). Hepatic function should be monitored closely with both clinical and laboratory follow-up for at least several months in patients who discontinue anti-hepatitis B therapy. If appropriate, initiation of anti‑hepatitis B therapy may be warranted [see Warnings and Precautions (5.2)].

Risk of HIV-1 Resistance if EPIVIR-HBV Is Used in Patients With Unrecognized or Untreated HIV-1 Infection: EPIVIR-HBV is not approved for the treatment of HIV-1 infection because the lamivudine dosage in EPIVIR-HBV is subtherapeutic and monotherapy is inappropriate for the treatment of HIV-1 infection. HIV-1 resistance may emerge in chronic hepatitis B-infected patients with unrecognized or untreated HIV-1 infection. Counseling and testing should be offered to all patients before beginning treatment with EPIVIR‑HBV and periodically during treatment [see Warnings and Precautions (5.3)].

1 INDICATIONS AND USAGE

EPIVIR-HBV is indicated for the treatment of chronic hepatitis B virus (HBV) infection associated with evidence of hepatitis B viral replication and active liver inflammation [see Clinical Studies (14.1, 14.2)].

The following points should be considered when initiating therapy with EPIVIR-HBV:

- Due to high rates of resistance development in treated patients, initiation of treatment with EPIVIR-HBV should only be considered when the use of an alternative antiviral agent with a higher genetic barrier to resistance is not available or appropriate.
- EPIVIR-HBV has not been evaluated in patients co-infected with HIV, hepatitis C virus (HCV), or hepatitis delta virus.
- EPIVIR-HBV has not been evaluated in liver transplant recipients or in patients with chronic hepatitis B virus infection with decompensated liver disease.
- EPIVIR-HBV has not been evaluated in pediatric patients younger than 2 years of age with chronic HBV infection.

DOSAGE AND ADMINISTRATION

2.1 HIV Counseling and Testing

HIV counseling and testing should be offered to all patients before beginning treatment with EPIVIR-HBV and periodically during treatment because of the risk of emergence of resistant-HIV-1 and limitation of treatment options if EPIVIR-HBV is prescribed to treat chronic hepatitis B infection in a patient who has unrecognized HIV-1 infection or acquires HIV-1 infection during treatment [see Warnings and Precautions (5.3)].

2.2 Dosage in Adult Patients

The recommended oral dosage of EPIVIR‑HBV is 100 mg once daily.

2.3 Dosage in Pediatric Patients

The recommended oral dosage of EPIVIR‑HBV for pediatric patients aged 2 to 17 years is 3 mg per kg once daily up to a maximum daily dosage of 100 mg. The oral solution formulation should be prescribed for patients requiring a dosage less than 100 mg or if unable to swallow tablets.

2.4 Dosage Adjustment in Adult Patients With Renal Impairment

Dosage recommendations for adult patients with reduced renal function are provided in Table 1 [see Clinical Pharmacology (12.3)].

Table 1. Dosage of EPIVIR-HBV in Adult Patients With Renal Impairment
Creatinine Clearance (mL/min) | Recommended Dosage of EPIVIR-HBV
≥50 | 100 mg once daily
30-49 | 100 mg first dose, then 50 mg once daily
15-29 | 100 mg first dose, then 25 mg once daily
5-14 | 35 mg first dose, then 15 mg once daily
<5 | 35 mg first dose, then 10 mg once daily

Following correction of the dosage for renal impairment, no additional dosage modification of EPIVIR-HBV is required after routine (4-hour) hemodialysis or peritoneal dialysis [see Clinical Pharmacology (12.3)].

There are insufficient data to recommend a specific dosage of EPIVIR-HBV in pediatric patients with renal impairment.

2.5 Important Administration Instructions

- EPIVIR-HBV tablets and oral solution may be administered with or without food.
- The tablets and oral solution may be used interchangeably [see Clinical Pharmacology (12.3)].
- The oral solution should be used for doses less than 100 mg.
- EPIVIR-HBV should not be used with other medications that contain lamivudine or medications that contain emtricitabine [see Warnings and Precautions (5.4)].

2.6 Assessing Patients During Treatment

Patients should be monitored regularly during treatment by a physician experienced in the management of chronic hepatitis B. During treatment, combinations of such events such as return of persistently elevated ALT, increasing levels of HBV DNA over time after an initial decline below assay limit, progression of clinical signs or symptoms of hepatic disease, and/or worsening of hepatic necroinflammatory findings may be considered as potentially reflecting loss of therapeutic response. Such observations should be taken into consideration when determining the advisability of continuing therapy with EPIVIR-HBV.

The optimal duration of treatment, the durability of HBeAg seroconversions occurring during treatment, and the relationship between treatment response and long‑term outcomes such as hepatocellular carcinoma or decompensated cirrhosis are not known.

3 DOSAGE FORMS AND STRENGTHS

- EPIVIR-HBV tablets: 100 mg, butterscotch-colored, film-coated, biconvex, capsule-shaped tablets imprinted with “GX CG5” on one side.
- EPIVIR-HBV oral solution: A clear, colorless to pale yellow, strawberry-banana–flavored liquid, containing 5 mg of lamivudine per 1 mL.

4 CONTRAINDICATIONS

EPIVIR-HBV is contraindicated in patients who have experienced a previous hypersensitivity reaction (e.g., anaphylaxis) to lamivudine or to any component of the tablets or oral solution.

WARNINGS AND PRECAUTIONS

5.1 Lactic Acidosis and Severe Hepatomegaly With Steatosis

Lactic acidosis and severe hepatomegaly with steatosis, including fatal cases, have been reported with the use of nucleoside analogues alone or in combination, including EPIVIR-HBV and other antiretrovirals. A majority of these cases have been in women. Obesity and prolonged nucleoside exposure may be risk factors. Most of these reports have described patients receiving nucleoside analogues for treatment of HIV infection, but there have been reports of lactic acidosis in patients receiving lamivudine for hepatitis B. Particular caution should be exercised when administering EPIVIR-HBV to any patient with known risk factors for liver disease; however, cases have also been reported in patients with no known risk factors. Treatment with EPIVIR-HBV should be suspended in any patient who develops clinical or laboratory findings suggestive of lactic acidosis or pronounced hepatotoxicity (which may include hepatomegaly and steatosis even in the absence of marked transaminase elevations).

5.2 Exacerbation of Hepatitis After Discontinuation of Treatment

Clinical and laboratory evidence of exacerbations of hepatitis have occurred after discontinuation of EPIVIR-HBV (these have been primarily detected by serum ALT elevations, in addition to the re-emergence of HBV DNA commonly observed after stopping treatment; see Table 4 for more information regarding frequency of posttreatment ALT elevations) [see Adverse Reactions (6.1)]. Although most events appear to have been self-limited, fatalities have been reported in some cases. The causal relationship of hepatitis exacerbation after discontinuation of EPIVIR-HBV has not been clearly established. Patients should be closely monitored with both clinical and laboratory follow-up for at least several months after stopping treatment with EPIVIR-HBV. There is insufficient evidence to determine whether re-initiation of EPIVIR-HBV alters the course of posttreatment exacerbations of hepatitis.

5.3 Risk of HIV-1 Resistance if EPIVIR-HBV Is Used in Patients With Unrecognized or Untreated HIV-1 Infection

EPIVIR-HBV tablets and oral solution contain a lower lamivudine dose than the lamivudine dose in the following drugs used to treat HIV-1 infection:

- EPIVIR® tablets and oral solution,
- COMBIVIR® (lamivudine/zidovudine) tablets,
- EPZICOM® (abacavir sulfate and lamivudine) tablets, and
- TRIZIVIR® (abacavir, lamivudine, and zidovudine) tablets

The formulation and dosage of lamivudine in EPIVIR-HBV are not approved for patients co-infected with HBV and HIV. If a decision is made to administer lamivudine to such patients, the higher dosage indicated for HIV therapy should be used as part of an appropriate combination regimen, and the prescribing information for EPIVIR, COMBIVIR, EPZICOM, or TRIZIVIR as well as for EPIVIR-HBV should be consulted. HIV counseling and testing should be offered to all patients before beginning EPIVIR-HBV and periodically during treatment because of the risk of rapid emergence of resistant HIV and limitation of treatment options if EPIVIR-HBV is prescribed to treat chronic hepatitis B in a patient who has unrecognized or untreated HIV-1 infection or acquires HIV-1 infection during treatment.

5.4 Coadministration With Other Medications Containing Lamivudine or Emtricitabine

Do not coadminister EPIVIR-HBV with other lamivudine-containing products including EPIVIR (lamivudine), COMBIVIR (lamivudine/zidovudine), EPZICOM (abacavir/lamivudine), or TRIZIVIR (abacavir/lamivudine/zidovudine).

Do not coadminister EPIVIR-HBV with emtricitabine-containing products including ATRIPLA® (efavirenz/emtricitabine/tenofovir disoproxil fumarate), COMPLERA® (rilpivirine/emtricitabine/tenofovir disoproxil fumarate), EMTRIVA® (emtricitabine), STRIBILD® (elvitegravir/cobicistat/emtricitabine/tenofovir disoproxil fumarate), or TRUVADA® (emtricitabine/tenofovir disoproxil fumarate).

5.5 Emergence of Resistance-Associated HBV Substitutions

In controlled clinical trials, YMDD-mutant HBV was detected in subjects with on-EPIVIR-HBV re-appearance of HBV DNA after an initial decline below the solution-hybridization assay limit [see Microbiology (12.4)]. Subjects treated with EPIVIR-HBV (adults and children) with YMDD-mutant HBV at 52 weeks showed diminished treatment responses in comparison with subjects treated with EPIVIR-HBV without evidence of YMDD substitutions, including the following: lower rates of HBeAg seroconversion and HBeAg loss (no greater than placebo recipients), more frequent return of positive HBV DNA, and more frequent ALT elevations. In the controlled trials, when subjects developed YMDD-mutant HBV, they had a rise in HBV DNA and ALT from their own previous on-treatment levels. Progression of hepatitis B, including death, has been reported in some subjects with YMDD-mutant HBV, including subjects from the liver transplant setting and from other clinical trials. In clinical practice, monitoring of ALT and HBV DNA levels during treatment with EPIVIR-HBV may aid in treatment decisions if emergence of viral mutants is suspected.

6 ADVERSE REACTIONS

The following adverse reactions are discussed in greater detail in other sections of the labeling:

- Lactic acidosis and severe hepatomegaly with steatosis [see Warnings and Precautions (5.1)].
- Exacerbation of hepatitis B after discontinuation of treatment [see Warnings and Precautions (5.2)].
- Risk of emergence of resistant HIV-1 infection [see Warnings and Precautions (5.3)].
- Risk of emergence of resistant HBV infection [see Warnings and Precautions (5.4)].

6.1 Clinical Trials Experience

Because clinical trials are conducted under widely varying conditions, adverse reaction rates observed in the clinical trials of a drug cannot be directly compared with rates in the clinical trials of another drug and may not reflect the rates observed in practice.

Adverse Reactions in Clinical Trials of Adults With Chronic Hepatitis B Virus Infection: Clinical adverse reactions (regardless of investigator’s causality assessment) reported in greater or equal to 10% of subjects who received EPIVIR-HBV and reported at a rate greater than placebo are listed in Table 2.

Table 2. Clinical Adverse Reactionsa Reported in ≥10% of Subjects who Received EPIVIR-HBV for 52 to 68 Weeks and at an Incidence Greater than Placebo (Trials 1-3)
Adverse Event | EPIVIR-HBV (n = 332) | Placebo (n = 200)
Ear, Nose, and Throat
Ear, nose, and throat infections | 25% | 21%
Sore throat | 13% | 8%
Gastrointestinal
Diarrhea | 14% | 12%

aIncludes adverse events regardless of severity and causality assessment.

Specified laboratory abnormalities reported in subjects who received EPIVIR-HBV and reported at a rate greater than in subjects who received placebo are listed in Table 3.

Table 3. Frequencies of Specified Laboratory Abnormalities Reported During Treatment at a Greater Frequency in Subjects Treated with EPIVIR-HBV Than With Placebo (Trials 1‑3)a
Test (Abnormal Level) | Subjects With Abnormality/Subjects With Observations
Test (Abnormal Level) | EPIVIR-HBV | Placebo
Serum Lipase ≥2.5 x ULNb | 10% | 7%
CPK ≥7 x baseline | 9% | 5%
Platelets <50,000/mm^3 | 4% | 3%

a Includes subjects treated for 52 to 68 weeks.

b Includes observations during and after treatment in the 2 placebo-controlled trials that collected this information.

ULN = Upper limit of normal.

In subjects followed for up to 16 weeks after discontinuation of treatment, posttreatment ALT elevations were observed more frequently in subjects who had received EPIVIR-HBV than in subjects who had received placebo. A comparison of ALT elevations between Weeks 52 and 68 in subjects who discontinued EPIVIR-HBV at Week 52 and subjects in the same trials who received placebo throughout the treatment course is shown in Table 4.

Table 4. Posttreatment ALT Elevations With No-Active-Treatment Follow-up (Trails 1 and 3)
Abnormal Value | Subjects With ALT Elevation/ Subjects With Observationsa
Abnormal Value | EPIVIR-HBVb | Placebob
ALT ≥2 x baseline value | 27% | 19%
ALT ≥3 x baseline valuec | 21% | 8%
ALT ≥2 x baseline value and absolute ALT >500 IU/L | 15% | 7%
ALT ≥2 x baseline value; and bilirubin >2 x ULN and ≥2 x baseline value | 0.7% | 0.9%

aEach subject may be represented in one or more category.

b During treatment phase.

cComparable to a Grade 3 toxicity in accordance with modified WHO criteria.

ULN = Upper limit of normal.

Adverse Reactions in Clinical Trials of Pediatric Subjects With Chronic Hepatitis B Virus Infection: Most commonly observed adverse reactions in the pediatric trials were similar to those in adult trials. Posttreatment transaminase elevations were observed in some subjects followed after cessation of EPIVIR-HBV.

6.2 Postmarketing Experience

In addition to adverse reactions reported from clinical trials, the following adverse reactions have been reported during postmarketing use of EPIVIR-HBV. Because these reactions are reported voluntarily from a population of unknown size, it is not always possible to reliably estimate the frequency or establish a causal relationship to drug exposure. These reactions have been chosen for inclusion due to a combination of their seriousness, frequency of reporting, or potential causal connection to lamivudine.

Blood and Lympatic System Disorders: Thrombocytopenia.

Digestive: Stomatitis.

Endocrine and Metabolic: Hyperglycemia.

General: Weakness.

Blood and Lymphatic: Anemia (including pure red cell aplasia and severe anemias progressing on therapy), lymphadenopathy, splenomegaly.

Hepatic and Pancreatic: Lactic acidosis and steatosis, posttreatment exacerbation of hepatitis [see Boxed Warning], pancreatitis.

Hypersensitivity: Anaphylaxis, urticaria.

Musculoskeletal: Cramps, rhabdomyolysis.

Nervous: Paresthesia, peripheral neuropathy.

Respiratory: Abnormal breath sounds/wheezing.

Skin: Alopecia, pruritus, rash.

7 DRUG INTERACTIONS

Lamivudine is predominantly eliminated in the urine by active organic cationic secretion. The possibility of interactions with other drugs administered concurrently should be considered, particularly when their main route of elimination is active renal secretion via the organic cationic transport system (e.g., trimethoprim). No data are available regarding interactions with other drugs that have renal clearance mechanisms similar to that of lamivudine.

8 USE IN SPECIFIC POPULATIONS

8.1 Pregnancy

Pregnancy Category C.

There are no adequate and well-controlled trials of EPIVIR-HBV in pregnant women. Because animal reproduction studies are not always predictive of human response, EPIVIR-HBV should be used during pregnancy only if the potential benefits outweigh the potential risks to the fetus.

Antiretroviral Pregnancy Registry: To monitor maternal-fetal outcomes of pregnant women exposed to lamivudine, a Pregnancy Registry has been established. Healthcare providers are encouraged to register patients by calling 1-800-258-4263.

Animal Data: Animal reproduction studies in rats and rabbits revealed no evidence of teratogenicity. Reproduction studies have been performed in rats and rabbits at orally administered doses up to 4,000 mg/kg/day and 1,000 mg/kg/day, respectively, producing plasma levels up to approximately 60 times that for the adult HBV dose. Evidence of early embryolethality was seen in the rabbit at exposure levels similar to those observed in humans, but there was no indication of this effect in the rat at exposure levels up to 60 times those in humans.

Studies in pregnant rats and rabbits showed that lamivudine is transferred to the fetus through the placenta.

8.3 Nursing Mothers

Lamivudine is excreted in human milk. Samples of breast milk obtained from 20 mothers receiving lamivudine monotherapy (300 mg twice daily, 6 times the recommended dosage for hepatitis B infection) or combination therapy (150 mg lamivudine twice daily [3 times the recommended dosage for hepatitis B infection] and 300 mg zidovudine twice daily) had measurable concentrations of lamivudine.

Because of the potential for serious adverse reactions in nursing infants, a decision should be made to discontinue EPIVIR-HBV taking into consideration the importance of continued hepatitis B therapy to the mother and the known benefits of breastfeeding.

8.4 Pediatric Use

EPIVIR-HBV is indicated for the treatment of chronic hepatitis B virus infection in pediatric patients aged 2 to 17 years [see Indications and Usage (1), Clinical Pharmacology (12.3), Clinical Studies (14.2)]. The safety and efficacy of EPIVIR-HBV in pediatric patients younger than 2 years have not been established.

8.5 Geriatric Use

Clinical trials of EPIVIR-HBV did not include sufficient numbers of subjects aged 65 and over to determine whether they respond differently from younger subjects. In general, dose selection for an elderly patient should be cautious, reflecting the greater frequency of decreased hepatic, renal, or cardiac function, and of concomitant disease or other drug therapy. In particular, because lamivudine is substantially excreted by the kidney and elderly patients are more likely to have decreased renal function, renal function should be monitored and dosage adjustments should be made accordingly [see Dosage and Administration (2.4), Clinical Pharmacology (12.4)].

8.6 Patients With Impaired Renal Function

Reduction of the dosage of EPIVIR-HBV is recommended for patients with impaired renal function [see Dosage and Administration (2.4), Clinical Pharmacology (12.3)].

8.7 Patients With Impaired Liver Function

No dose adjustment for lamivudine is required for patients with impaired hepatic function.

10 OVERDOSAGE

There is no known antidote for EPIVIR-HBV. If overdose occurs, the patient should be monitored, and standard supportive treatment utilized, as required.

Because a negligible amount of lamivudine was removed via (4-hour) hemodialysis, continuous ambulatory peritoneal dialysis, and automated peritoneal dialysis, it is not known if continuous hemodialysis would provide clinical benefit in a lamivudine overdose event.

11 DESCRIPTION

EPIVIR-HBV is a synthetic nucleoside analogue with activity against HBV. The chemical name of lamivudine is (2R,cis)-4-amino-1-(2-hydroxymethyl-1,3-oxathiolan-5-yl)-(1H)-pyrimidin-2-one. Lamivudine is the (-)enantiomer of a dideoxy analogue of cytidine. Lamivudine has also been referred to as (-)2′,3′-dideoxy, 3′-thiacytidine. It has a molecular formula of C8H11N3O3S and a molecular weight of 229.3. It has the following structural formula:

Lamivudine is a white to off-white crystalline solid with a solubility of approximately 70 mg per mL in water at 20°C.

EPIVIR-HBV tablets are for oral administration. Each tablet contains 100 mg of lamivudine and the inactive ingredients hypromellose, macrogol 400, magnesium stearate, microcrystalline cellulose, polysorbate 80, red iron oxide, sodium starch glycolate, titanium dioxide, and yellow iron oxide.

EPIVIR-HBV oral solution is for oral administration. One milliliter (1 mL) of EPIVIR-HBV oral solution contains 5 mg of lamivudine (5 mg per mL) in an aqueous solution and the inactive ingredients artificial strawberry and banana flavors, citric acid (anhydrous), methylparaben, propylene glycol, propylparaben, sodium citrate (dihydrate), and sucrose (200 mg).

12 CLINICAL PHARMACOLOGY

12.1 Mechanism of Action

Lamivudine is an antiviral agent [see Microbiology (12.4)].

12.3 Pharmacokinetics

Pharmacokinetics in Adults: The pharmacokinetic properties of lamivudine have been studied as single and multiple oral doses ranging from 5 mg to 600 mg per day administered to HBV-infected patients.

Absorption and Bioavailability: Following single oral doses of 100 mg, the peak serum lamivudine concentration (Cmax) in HBV-infected patients (steady state) and healthy subjects (single dose) was 1.28 ± 0.56 mcg per mL and 1.05 ± 0.32 mcg per mL (mean ± SD), respectively, which occurred between 0.5 and 2 hours after administration. The area under the plasma concentration versus time curve (AUC[0-24 h]) following 100 mg lamivudine oral single and repeated daily doses to steady state was 4.3 ± 1.4 (mean ± SD) and 4.7 ± 1.7 mcg•hour per mL, respectively. The relative bioavailability of the tablet and oral solution were demonstrated in healthy subjects. Although the solution demonstrated a slightly higher peak serum concentration (Cmax), there was no significant difference in systemic exposure (AUC) between the oral solution and the tablet. Therefore, the oral solution and the tablet may be used interchangeably.

After oral administration of lamivudine once daily to HBV-infected adults, the AUC and Cmax increased in proportion to dose over the range from 5 mg to 600 mg once daily.

Absolute bioavailability in 12 adult subjects was 86% ± 16% (mean ± SD) for the 150-mg tablet and 87% ± 13% for the 10-mg per mL oral solution.

Effects of Food on Oral Absorption: The 100-mg tablet was administered orally to 24 healthy subjects on 2 occasions, once in the fasted state and once with food (standard meal: 967 kcal; 67 grams fat, 33 grams protein, 58 grams carbohydrate). There was no significant difference in systemic exposure (AUC) in the fed and fasted states.

Distribution: The apparent volume of distribution after IV administration of lamivudine to 20 asymptomatic HIV-1-infected subjects was 1.3 ± 0.4 L per kg, suggesting that lamivudine distributes into extravascular spaces. Volume of distribution was independent of dose and did not correlate with body weight.

Binding of lamivudine to human plasma proteins is less than 36% and independent of dose. In vitro studies showed that over the concentration range of 0.1 to 100 mcg per mL, the amount of lamivudine associated with erythrocytes ranged from 53% to 57% and was independent of concentration.

Metabolism: Metabolism of lamivudine is a minor route of elimination. In humans, the only known metabolite of lamivudine is the trans-sulfoxide metabolite. In 9 healthy subjects receiving 300 mg of lamivudine as single oral doses, a total of 4.2% (range 1.5% to 7.5%) of the dose was excreted as the trans-sulfoxide metabolite in the urine, the majority of which was excreted in the first 12 hours. Serum concentrations of the trans-sulfoxide metabolite have not been determined.

Elimination: The majority of lamivudine is eliminated unchanged in urine by active organic cationic secretion. In 9 healthy subjects given a single 300-mg oral dose of lamivudine, renal clearance was 199.7 ± 56.9 mL per min (mean ± SD). In 20 HIV-1-infected subjects given a single IV dose, renal clearance was 280.4 ± 75.2 mL per min (mean ± SD), representing 71% ± 16% (mean ± SD) of total clearance of lamivudine.

In most single-dose trials in HIV-1-infected subjects, HBV-infected subjects, or healthy subjects with serum sampling for 24 hours after dosing, the observed mean elimination half-life (t½) ranged from 5 to 7 hours. In HIV-1-infected subjects, total clearance was 398.5 ± 69.1 mL per min (mean ± SD). Oral clearance and elimination half-life were independent of dose and body weight over an oral dosing range of 0.25 to 10 mg per kg.

Special Populations: Adults With Renal Impairment: The pharmacokinetic properties of lamivudine have been determined in healthy subjects and in subjects with impaired renal function, with and without hemodialysis (Table 5).

Table 5. Pharmacokinetic Parameters (Mean ± SD) Dose-Normalized to a Single 100-mg Oral Dose of Lamivudine in Subjects With Varying Degrees of Renal Function
Parameter | Creatinine Clearance Criterion; (Number of Subjects)
Parameter | ≥80 mL/min; (n = 9) | 20-59 mL/min (n = 8) | <20 mL/min; (n = 6)
Creatinine clearance (mL/min) | 97; (range 82-117) | 39; (range 25-49) | 15; (range 13-19)
Cmax (mcg/mL) | 1.31 ± 0.35 | 1.85 ± 0.40 | 1.55 ± 0.31
AUC (mcg•h/mL) | 5.28 ± 1.01 | 14.67 ± 3.74 | 27.33 ± 6.56
Cl/F (mL/min) | 326.4 ± 63.8 | 120.1 ± 29.5 | 64.5 ± 18.3

Exposure (AUC), Cmax, and half-life increased with diminishing renal function (as expressed by creatinine clearance). Apparent total oral clearance (Cl/F) of lamivudine decreased as creatinine clearance decreased. Tmax was not significantly affected by renal function. Based on these observations, it is recommended that the dosage of lamivudine be modified in patients with renal impairment [see Dosage and Administration (2.4)].

Hemodialysis increases lamivudine clearance from a mean of 64 to 88 mL per min; however, the length of time of hemodialysis (4 hours) was insufficient to significantly alter mean lamivudine exposure after a single-dose administration. Continuous ambulatory peritoneal dialysis and automated peritoneal dialysis have negligible effects on lamivudine clearance. Therefore, it is recommended, following correction of dose for creatinine clearance, that no additional dose modification be made after routine hemodialysis or peritoneal dialysis.

It is not known whether lamivudine can be removed by continuous (24-hour) hemodialysis.

Pediatric Patients With Renal Impairment: The effect of renal impairment on lamivudine pharmacokinetics in pediatric patients with chronic hepatitis B is not known.

Adults With Hepatic Impairment: The pharmacokinetic properties of lamivudine in adults with hepatic impairment are shown in Table 6. Subjects were stratified by severity of hepatic impairment.

Table 6. Pharmacokinetic Parameters (Mean ± SD) Dose-Normalized to a Single 100-mg Dose of Lamivudine in Subjects With Normal or Impaired Hepatic Function
Parameter | Normal; (n = 8) | Impairmenta
Parameter | Normal; (n = 8) | Moderate; (n = 8) | Severe; (n = 8)
Cmax (mcg/mL) | 0.92 ± 0.31 | 1.06 ± 0.58 | 1.08 ± 0.27
AUC (mcg•h/mL) | 3.96 ± 0.58 | 3.97 ± 1.36 | 4.30 ± 0.63
Tmax(h) | 1.3 ± 0.8 | 1.4 ± 0.8 | 1.4 ± 1.2
Cl/F (mL/min) | 424.7 ± 61.9 | 456.9 ± 129.8 | 395.2 ± 51.8
Clr (mL/min) | 279.2 ± 79.2 | 323.5 ± 100.9 | 216.1 ± 58.0

aHepatic impairment assessed by aminopyrine breath test.

Pharmacokinetic parameters were not altered by diminishing hepatic impairment. Therefore, no dose adjustment for lamivudine is required for patients with impaired hepatic function. Safety and efficacy of EPIVIR-HBV have not been established in the presence of decompensated liver disease [see Indications and Usage (1)].

Adults Post-Hepatic Transplant: Fourteen HBV-infected subjects received liver transplant following lamivudine therapy and completed pharmacokinetic assessments at enrollment, 2 weeks after 100-mg once-daily dosing (pre-transplant), and 3 months following transplant; there were no significant differences in pharmacokinetic parameters. The overall exposure of lamivudine is primarily affected by renal impairment; consequently, transplant patients with renal impairment had generally higher exposure than patients with normal renal function. Safety and efficacy of EPIVIR-HBV have not been established in this population [see Indications and Usage (1)].

Pediatric Subjects: Lamivudine pharmacokinetics were evaluated in a 28-day dose-ranging trial in 53 pediatric subjects with chronic hepatitis B. Subjects aged 2 to 12 years were randomized to receive lamivudine 0.35 mg per kg twice daily, 3 mg per kg once daily, 1.5 mg per kg twice daily, or 4 mg per kg twice daily. Subjects aged 13 to 17 years received lamivudine 100 mg once daily. Lamivudine Tmax was 0.5 to 1 hour. In general, both Cmax and exposure (AUC) showed dose proportionality in the dosing range studied. Weight-corrected oral clearance was highest at age 2 and declined from 2 to 12 years, where values were then similar to those seen in adults. A dose of 3 mg per kg given once daily produced a steady-state lamivudine AUC (mean 5,953 ng•hour per mL ± 1,562 SD) similar to that associated with a dose of 100 mg per day in adults.

Gender: There are no significant gender differences in lamivudine pharmacokinetics.

Race: There are no significant racial differences in lamivudine pharmacokinetics.

Drug Interactions: Interferon Alfa: Multiple doses of lamivudine and a single dose of interferon were coadministered to 19 healthy male subjects in a pharmacokinetics study. Results indicated a 10% reduction in lamivudine AUC, but no change in interferon pharmacokinetic parameters when the 2 drugs were given in combination. All other pharmacokinetic parameters (Cmax, Tmax, and t½) were unchanged. There was no significant pharmacokinetic interaction between lamivudine and interferon alfa in this trial.

Ribavirin: In vitro data indicate ribavirin reduces phosphorylation of lamivudine, stavudine, and zidovudine. However, no pharmacokinetic (e.g., plasma concentrations or intracellular triphosphorylated active metabolite concentrations) or pharmacodynamic (e.g., loss of HIV-1/HCV virologic suppression) interaction was observed when ribavirin and lamivudine (n = 18), stavudine (n = 10), or zidovudine (n = 6) were coadministered as part of a multi-drug regimen to HIV‑1/HCV co-infected subjects.

Trimethoprim/Sulfamethoxazole: Lamivudine and trimethoprim/sulfamethoxazole (TMP/SMX) were coadministered to 14 HIV-positive subjects in a single-center, open-label, randomized, crossover trial. Each subject received treatment with a single 300-mg dose of lamivudine and TMP 160 mg/SMX 800 mg once a day for 5 days with concomitant administration of lamivudine 300 mg with the fifth dose in a crossover design. Coadministration of TMP/SMX with lamivudine resulted in an increase of 44% ± 23% (mean ± SD) in lamivudine AUC, a decrease of 29% ± 13% in lamivudine oral clearance, and a decrease of 30% ± 36% in lamivudine renal clearance. The pharmacokinetic properties of TMP and SMX were not altered by coadministration with lamivudine.

Zidovudine: Lamivudine and zidovudine were coadministered to 12 asymptomatic HIV-positive adult subjects in a single-center, open-label, randomized, crossover trial. No significant differences were observed in AUC or total clearance for lamivudine or zidovudine when the 2 drugs were administered together. Coadministration of lamivudine with zidovudine resulted in an increase of 39% ± 62% (mean ± SD) in Cmax of zidovudine.

12.4 Microbiology

Mechanism of Action: Lamivudine is a synthetic nucleoside analogue. Intracellularly, lamivudine is phosphorylated to its active 5′-triphosphate metabolite, lamivudine triphosphate, 3TC-TP. The principal mode of action of 3TC-TP is the inhibition of the RNA- and DNA- dependent polymerase activities of HBV reverse transcriptase (rt) via DNA chain termination after incorporation of the nucleotide analogue into viral DNA. 3TC-TP is a weak inhibitor of mammalian α, β, and γ-DNA polymerases.

Antiviral Activity: Activity of lamivudine against HBV in cell culture was assessed in HBV DNA-transfected 2.2.15 cells, HB611 cells, and infected human primary hepatocytes. EC50 values (the concentration of drug needed to reduce the level of extracellular HBV DNA by 50%) varied from 0.01 μM (2.3 ng per mL) to 5.6 μM (1.3 mcg per mL) depending upon the duration of exposure of cells to lamivudine, the cell model system, and the protocol used. See the EPIVIR prescribing information for information regarding activity of lamivudine against HIV

Resistance: Lamivudine-resistant isolates were identified in subjects with virologic breakthrough, defined when using solution hybridization assay as the detection of HBV DNA in serum on 2 or more occasions after failing to detect HBV DNA on 2 or more occasions and defined when using PCR assay as a greater than 1 log10 (10-fold) increase in serum HBV DNA from nadir during treatment in a subject who had an initial virologic response.

Lamivudine-resistant HBV isolates develop rtM204V/I substitutions in the YMDD motif of the catalytic domain of the viral reverse transcriptase. rtM204V/I substitutions are frequently accompanied by other substitutions (rtV173L, rtL180M) which enhance the level of lamivudine resistance or act as compensatory substitutions improving replication efficiency. Other substitutions detected in lamivudine-resistant HBV isolates include rtL80I and rtA181T.

In 4 controlled clinical trials in adults with HBeAg-positive chronic hepatitis B virus infection (CHB), YMDD-mutant HBV was detected in 81 of 335 subjects receiving EPIVIR-HBV 100 mg once daily for 52 weeks. The prevalence of YMDD substitutions was less than 10% in each of these trials for subjects studied at 24 weeks and increased to an average of 24% (range in 4 trials: 16% to 32%) at 52 weeks. In limited data from a long-term follow-up trial in subjects who continued 100 mg per day EPIVIR-HBV after one of these trials, YMDD substitutions further increased from 18% (10 of 57) at 1 year to 41% (20 of 49), 53% (27 of 51), and 69% (31 of 45) after 2, 3, and 4 years of treatment, respectively. Over the 5-year treatment period, the proportion of subjects who developed YMDD-mutant HBV at any time was 69% (40 of 58).

In a controlled trial, treatment-naive subjects with HBeAg-positive CHB were treated with EPIVIR-HBV or EPIVIR-HBV plus adefovir dipivoxil combination therapy. Following 104 weeks of therapy, YMDD-mutant HBV was detected in 7 of 40 (18%) subjects receiving combination therapy compared with 15 of 35 (43%) subjects receiving therapy with only EPIVIR-HBV. In another controlled trial, combination therapy was evaluated in adult subjects with HBeAg-positive CHB who had YMDD-mutant HBV and diminished clinical and virologic response to EPIVIR-HBV. Following 52 weeks of EPIVIR-HBV plus adefovir dipivoxil combination therapy (n = 46) or therapy with only EPIVIR-HBV (n = 49), YMDD‑mutant HBV was detected less frequently in subjects receiving combination therapy, 62% versus 96.

A published trial suggested that the rates of lamivudine resistance in subjects treated for HBeAg-negative CHB appear to be more variable (0% to 27% at 1 year and 10% to 56% at 2 years).

Pediatric Subjects: In a controlled trial in pediatric subjects, YMDD-mutant HBV was detected in 31 of 166 (19%) subjects receiving EPIVIR-HBV for 52 weeks. For a subgroup that remained on therapy with EPIVIR-HBV in a follow-up trial, YMDD substitutions increased from 24% (29 of 121) at 12 months to 59% (68 of 115) at 24 months and 64% (66 of 103) at 36 months of treatment with EPIVIR-HBV.

Cross-Resistance: HBV containing lamivudine resistance-associated substitutions (rtL180M, rtM204I, rtM204V, rtL180M and rtM204V, rtV173L and rtL180M and rtM204V) retain susceptibility to adefovir dipivoxil but have reduced susceptibility to entecavir (30 fold) and telbivudine (greater than 100 fold). The lamivudine resistance-associated substitution rtA181T results in diminished response to adefovir and telbivudine. Similarly, HBV with entecavir resistance-associated substitutions (I169T/M250V and T184G/S202I) have greater than 1,000-fold reductions in susceptibility to lamivudine.

13 NONCLINICAL TOXICOLOGY

13.1 Carcinogenesis, Mutagenesis, Impairment of Fertility

Carcinogenesis: Long-term carcinogenicity studies with lamivudine in mice and rats showed no evidence of carcinogenic potential at exposures up to 34 times (mice) and 200 times (rats) those observed in humans at the recommended therapeutic dose for chronic hepatitis B.

Mutagenesis: Lamivudine was not active in a microbial mutagenicity screen or an in vitro cell transformation assay, but showed weak in vitro mutagenic activity in a cytogenetic assay using cultured human lymphocytes and in the mouse lymphoma assay. However, lamivudine showed no evidence of in vivo genotoxic activity in the rat at oral doses of up to 2,000 mg per kg producing plasma levels of 60 to 70 times those in humans at the recommended dose for chronic hepatitis B.

Impairment of Fertility: In a study of reproductive performance, lamivudine administered to rats at doses up to 4,000 mg per kg per day, producing plasma levels 80 to 120 times those in humans, revealed no evidence of impaired fertility and no effect on the survival, growth, and development to weaning of the offspring.

14 CLINICAL STUDIES

14.1 Clinical Studies of EPIVIR-HBV in Adult Patients

The safety and efficacy of EPIVIR-HBV 100 mg once daily versus placebo were evaluated in 3 controlled trials in subjects with compensated chronic hepatitis B virus infection. All subjects were aged 16 years or older and had chronic hepatitis B virus infection (serum HBsAg-positive for at least 6 months) accompanied by evidence of HBV replication (serum HBeAg-positive and positive for serum HBV DNA) and persistently elevated ALT levels and/or chronic inflammation on liver biopsy compatible with a diagnosis of chronic viral hepatitis. The results of these trials are summarized below.

- Trial 1 was a randomized, double-blind trial of EPIVIR-HBV 100 mg once daily versus placebo for 52 weeks followed by a 16-week no-treatment period in 141 treatment-naive US subjects.
- Trial 2 was a randomized, double-blind, 3-arm trial that compared EPIVIR-HBV 25 mg once daily versus EPIVIR-HBV 100 mg once daily versus placebo for 52 weeks in 358 Asian subjects.
- Trial 3 was a randomized, partially-blind trial conducted primarily in North America and Europe in 238 subjects who had ongoing evidence of active chronic hepatitis B despite previous treatment with interferon alfa. The trial compared EPIVIR-HBV 100 mg once daily for 52 weeks, followed by either EPIVIR-HBV 100 mg or matching placebo once daily for 16 weeks (Arm 1), versus placebo once daily for 68 weeks (Arm 2).

Principal endpoint comparisons for the histologic and serologic outcomes in subjects receiving EPIVIR- HBV (100 mg daily) or placebo in these trials are shown in the following tables.

Table 7. Histologic Response at Week 52 Among Adult Subjects Receiving EPIVIR-HBV 100 mg Once Daily or Placebo
Assessment | Trial 1 |  | Trial 2 |  | Trial 3
Assessment | EPIVIR-HBV; (n = 62) | Placebo; (n = 63) | EPIVIR-HBV; (n = 131) | Placebo; (n = 68) | EPIVIR-HBV; (n = 110) | Placebo; (n = 54)
Improvementa | 55% | 25% | 56% | 26% | 56% | 26%
No Improvement | 27% | 59% | 36% | 62% | 25% | 54%
Missing Data | 18% | 16% | 8% | 12% | 19% | 20%

aImprovement was defined as a greater than or equal to 2-point decrease in the Knodell Histologic Activity Index (HAI) at Week 52 compared with pretreatment HAI. Subjects with missing data at baseline were excluded.

Table 8. HBeAg Seroconvertersa at Week 52 Among Adult Subjects Receiving EPIVIR-HBV 100 mg Once Daily or Placebo
Seroconversion | Trial 1 |  | Trial 2 |  | Trial 3
Seroconversion | EPIVIR-HBV; (n = 63) | Placebo; (n = 69) | EPIVIR-HBV; (n = 140) | Placebo; (n = 70) | EPIVIR-HBV; (n = 108) | Placebo; (n = 53)
Seroconverters | 17% | 6% | 16% | 4% | 15% | 13%

a Three-component seroconversion was defined as Week 52 values showing loss of HBeAg, gain of HBeAb, and reduction of HBV DNA to below the solution-hybridization assay limit. Subjects with negative baseline HBeAg or HBV DNA assay were excluded from the analysis.

Normalization of serum ALT levels was more frequent with EPIVIR-HBV treatment compared with placebo in Trials 1-3.

The majority of subjects treated with EPIVIR-HBV showed a decrease of HBV DNA to below the assay limit early in the course of therapy. However, reappearance of assay-detectable HBV DNA during treatment with EPIVIR-HBV was observed in approximately one-third of subjects after this initial response.

14.2 Clinical Studies of EPIVIR-HBV in Pediatric Subjects

The safety and efficacy of EPIVIR-HBV were evaluated in a double-blind clinical trial in 286 subjects aged from 2 to 17 years, who were randomized (2:1) to receive 52 weeks of EPIVIR-HBV (3 mg per kg once daily to a maximum of 100 mg once daily) or placebo. All subjects had compensated chronic hepatitis B accompanied by evidence of hepatitis B virus replication (positive serum HBeAg and positive for serum HBV DNA by a research branched-chain DNA assay) and persistently elevated serum ALT levels. The combination of loss of HBeAg and reduction of HBV DNA to below the assay limit of the research assay, evaluated at Week 52, was observed in 23% of subjects treated with EPIVIR-HBV and 13% of placebo-treated subjects. Normalization of serum ALT was achieved and maintained to Week 52 more frequently in subjects treated with EPIVIR-HBV compared with placebo (55% versus 13%). As in the adult controlled trials, most subjects treated with EPIVIR-HBV had decreases in HBV DNA below the assay limit early in treatment, but about one third of subjects with this initial response had reappearance of assay-detectable HBV DNA during treatment. Adolescents (aged 13 to 17 years) showed less evidence of treatment effect than younger pediatric subjects.

16 HOW SUPPLIED/STORAGE AND HANDLING

EPIVIR-HBV tablets, 100 mg, are butterscotch-colored, film-coated, biconvex, capsule-shaped tablets imprinted with “GX CG5” on one side.

They are supplied by State of Florida DOH Central Pharmacy as follows:

NDC | Strength | Quantity/Form | Color | Source Prod. Code
53808-0893-1 | 100 MG | 30 Tablets in a Blister Pack | butterscotch-colored | 0173-0662

Store at 25°C (77°F), excursions permitted to 15° to 30°C (59° to 86°F) [see USP Controlled Room Temperature].

17 PATIENT COUNSELING INFORMATION

Advise the patient to read the FDA-approved patient labeling (Patient Information).

Advice for the Patient

- Advise patients to remain under the care of a physician while taking EPIVIR-HBV and discuss any new symptoms or concurrent medications with their physician.
- Advise patients that EPIVIR-HBV is not a cure for hepatitis B, that the long-term treatment benefits of EPIVIR-HBV are unknown at this time, and, in particular, that the relationship of initial treatment response to outcomes such as hepatocellular carcinoma and decompensated cirrhosis is unknown [see Dosage and Administration (2.6)].
- Inform patients that deterioration of liver disease has occurred in some cases when treatment was discontinued. Instruct patients to discuss any changes in regimen with their physician [see Warnings and Precautions (5.2)].
- Inform patients that emergence of resistant hepatitis B virus and worsening of disease can occur during treatment, and they should promptly report any new symptoms to their physician [see Warnings and Precautions (5.5)].
- Counsel patients on the importance of testing for HIV to avoid inappropriate therapy and development of resistant HIV. HIV counseling and testing should be offered before starting EPIVIR-HBV and periodically during therapy.
- Advise patients that EPIVIR-HBV tablets and EPIVIR-HBV oral solution contain a lower dose of the same active ingredient (lamivudine) as EPIVIR tablets, EPIVIR oral solution, COMBIVIR tablets, EPZICOM tablets, and TRIZIVIR tablets. EPIVIR-HBV should not be taken concurrently with EPIVIR, COMBIVIR, EPZICOM, or TRIZIVIR [see Dosage and Administration (2.1), Warnings and Precautions (5.3, 5.4)].
- Advise patients not to take EPIVIR-HBV with emtricitabine-containing medicines, such as ATRIPLA, COMPLERA, EMTRIVA, STRIBILD, or TRUVADA [see Warnings and Precautions (5.4)].
- Advise patients that treatment with EPIVIR-HBV has not been shown to reduce the risk of transmission of HBV to others through sexual contact or blood contamination [see Use in Specific Populations (8.1)].
  ∘ Do not share needles or other injection equipment.
  ∘ Do not share personal items that can have blood or body fluids on them, like toothbrushes and razor blades.
  ∘ Do not have any kind of sex without protection. Always practice safe sex by using a latex or polyurethane condom to lower the chance of sexual contact with semen, vaginal secretions, or blood.
- Advise diabetic patients that each 20-mL dose of EPIVIR-HBV oral solution contains 4 grams of sucrose [see Description (11)].

EPIVIR-HBV is a registered trademark of the GlaxoSmithKline group of companies.

EPIVIR, COMBIVIR, EPZICOM, and TRIZIVIR are registered trademarks of the ViiV Healthcare group of companies.

The other brands listed are trademarks of their respective owners and are not trademarks of the GlaxoSmithKline group of companies. The makers of these brands are not affiliated with and do not endorse the GlaxoSmithKline group of companies or its products.

GlaxoSmithKline

Research Triangle Park, NC 27709

Manufactured under agreement from

Shire Pharmaceuticals Group plc

Basingstoke, UK

©2013, GlaxoSmithKline group of companies. All rights reserved.

Patient Information

EPIVIR HBV® (EP-i-veer h-b-v)

(lamivudine)

tablets

EPIVIR HBV® (EP-i-veer h-b-v)

(lamivudine)

oral solution

Read this Patient Information before you start taking EPIVIR-HBV and each time you get a refill. There may be new information. This information does not take the place of talking with your healthcare provider about your medical condition or treatment.

What is the most important information I should know about EPIVIR-HBV?

EPIVIR-HBV can cause serious side effects, including:

Build-up of an acid in your blood (lactic acidosis).Lactic acidosis can happen in some people who take EPIVIR-HBV or similar (nucleoside analogs) medicines. Lactic acidosis is a serious medical emergency that can lead to death.

Lactic acidosis can be hard to identify early because the symptoms could seem like symptoms of other health problems. Call your healthcare provider right away if you get any of the following symptoms that could be signs of lactic acidosis:

- feel very weak or tired
- unusual (not normal) muscle pain
- trouble breathing
- stomach pain with nausea and vomiting
- feel cold, especially in your arms and legs
- feel dizzy or light-headed
- have a fast or irregular heartbeat

Severe liver problems.Severe liver problems can happen in people who take EPIVIR-HBV or similar medicines. In some cases these liver problems can lead to death. Your liver may become large (hepatomegaly) and you may develop fat in your liver (steatosis) when you take EPIVIR-HBV. Call your healthcare provider right away if you get any of the following signs of liver problems:

- your skin or the white part of your eyes turns yellow (jaundice)
- dark “tea-colored” urine
- light-colored bowel movements (stools)
- loss of appetite for several days or longer
- nausea
- stomach pain

You may be more likely to get lactic acidosis or severe liver problems if you are female, very overweight, or have been taking nucleoside analogue medicines for a long time.

Worsening liver disease.Your hepatitis B infection may become worse after stopping treatment with EPIVIR-HBV. Worsening liver disease can be serious and may lead to death. If you stop treatment with EPIVIR-HBV, your healthcare provider will need to check your health and do blood tests to check your liver for at least several months after you stop taking EPIVIR-HBV.

Risk of HIV-1 resistance in people with unknown HIV-1 infection or in people with untreated HIV-1 infection.If you have or get HIV that is not being treated with medicines while taking EPIVIR-HBV, the HIV virus may develop resistance to certain HIV medicines and become harder to treat.

- Your healthcare provider should offer you counseling and testing for HIV-1 infection before you start treatment for hepatitis B with EPIVIR-HBV and during treatment.
- EPIVIR-HBV tablets and EPIVIR‑HBV oral solution contain a lower dose of lamivudine than other medicines that contain lamivudine and are used to treat HIV-1 infection. See “What should I tell my healthcare provider?” for a list of medicines you should not take with EPIVIR-HBV.

Resistant Hepatitis B Virus (HBV).The hepatitis B virus can change (mutate) during your treatment with EPIVIR-HBV and become harder to treat (resistant). If this happens, your liver disease can become worse and may lead to death. Tell your healthcare provider right away if you have any new symptoms.

What is EPIVIR-HBV?

EPIVIR-HBV is a prescription medicine used to treat long-term (chronic) hepatitis B virus (HBV) when the disease is progressing and there is liver swelling (inflammation).

- EPIVIR-HBV will not cure HBV.
- EPIVIR-HBV may lower the amount of HBV in your body.
- EPIVIR-HBV may lower the ability of HBV to multiply and infect new liver cells.
- EPIVIR-HBV may improve the condition of your liver.
- The long-term benefits of taking EPIVIR-HBV for treatment of chronic hepatitis B infection are not known.

It is not known if EPIVIR-HBV is safe and effective in:

- people with chronic HBV who have a severely damaged liver that is unable to work properly (decompensated liver disease)
- people with hepatitis C virus or hepatitis D (delta) virus
- people who have had a liver transplant
- children with chronic HBV less than 2 years of age

EPIVIR-HBV does not stop you from spreading HBV to others by sex, sharing needles, or being exposed to your blood. Avoid doing things that can spread HBV infection to others.

- Do not share or re-use needles or other injection equipment.
- Do not share personal items that can have blood or body fluids on them, like toothbrushes and razor blades.
- Do not have any kind of sex without protection. Always practice safer sex by using a latex or polyurethane condom to lower the chance of sexual contact with semen, vaginal secretions, or blood.

A vaccine is available to protect people at risk for becoming infected with HBV. You can ask your healthcare provider for information about this vaccine.

Who should not take EPIVIR-HBV?

Do not take EPIVIR-HBV if you are allergic to lamivudine or any of the ingredients in EPIVIR-HBV. See the end of this leaflet for a complete list of ingredients in EPIVIR-HBV.

What should I tell my healthcare provider before taking EPIVIR-HBV?

Before you take EPIVIR-HBV, tell your healthcare provider if you:

- have HIV-1 infection.
- have kidney problems
- have diabetes. Each 20-mL dose (100 mg) of EPIVIR-HBV oral solution contains 4 grams of sucrose.
- have any other medical condition
- are pregnant or plan to become pregnant. It is not known if EPIVIR-HBV will harm your unborn baby.
Pregnancy Registry. There is a pregnancy registry for women who take antiviral medicines during pregnancy. The purpose of this registry is to collect information about the health of you and your baby. Talk to your healthcare provider about how you can take part in this registry.

- are breastfeeding or plan to breastfeed. EPIVIR-HBV can pass into your breast milk and may harm your baby. You and your healthcare provider should decide if you will take EPIVIR-HBV or breastfeed.

Tell your healthcare provider about all the medicines you take, including prescription and over-the-counter medicines, vitamins,and herbal supplements.

Do not take EPIVIR-HBV if you also take:

- other medicines that contain lamivudine (COMBIVIR®, EPIVIR®, EPZICOM®, TRIZIVIR®)
- medicines that contain emtricitabine (ATRIPLA®, COMPLERA®, EMTRIVA®, STRIBILD®, TRUVADA®)

How should I take EPIVIR-HBV?

- Take EPIVIR-HBV exactly as your healthcare provider tells you to take it.
- Do not change your dose or stop taking EPIVIR-HBV without talking with your healthcare provider.
- EPIVIR-HBV is taken 1 time each day.
- Your healthcare provider may prescribe a lower dose if you have problems with your kidneys.
- For children 2 to 17 years of age, your healthcare provider will prescribe the right dose of EPIVIR-HBV based on your child’s body weight.
- Take EPIVIR-HBV by mouth, with or without food.
- Tell your healthcare provider if you have trouble swallowing tablets. EPIVIR-HBV also comes as a liquid (oral solution).
- If you take too much EPIVIR-HBV, call your healthcare provider or go to the nearest hospital emergency room right away.
- It is important to stay under your healthcare provider’s care while taking EPIVIR-HBV. Tell your healthcare provider about any new symptoms that you have.

What are the possible side effects of EPIVIR-HBV?

EPIVIR-HBV may cause serious side effects, including:

See "What is the most important information I should know about EPIVIR-HBV?".

The most common side effects of EPIVIR-HBV include:

- ear, nose, and throat infections
- sore throat
- diarrhea

Tell your healthcare provider if you have any side effect that bothers you or that does not go away.

These are not all the possible side effects of EPIVIR-HBV. For more information, ask your healthcare provider or pharmacist.

Call your doctor for medical advice about side effects. You may report side effects to FDA at 1-800-FDA-1088.

How should I store EPIVIR-HBV?

- Store EPIVIR‑HBV tablets and oral solution at room temperature between 68°F to 77°F (20°C to 25°C).
- Keep bottles of EPIVIR-HBV oral solution tightly closed.

Keep EPIVIR-HBV and all medicines out of the reach of children.

General information about the safe and effective use of EPIVIR-HBV

Medicines are sometimes prescribed for purposes other than those listed in a Patient Information leaflet. Do not use EPIVIR-HBV for a condition for which it was not prescribed. Do not give EPIVIR-HBV to other people, even if they have the same symptoms that you have. It may harm them.

If you would like more information, talk with your healthcare provider. You can ask your pharmacist or healthcare provider for information about EPIVIR-HBV that is written for health professionals.

For more information, go to www.gsk.com or call 1-800-25-5249.

What are the ingredients in EPIVIR-HBV?

Active ingredient: lamivudine.

Inactive ingredients:

EPIVIR-HBVtablets: hypromellose, macrogol 400, magnesium stearate, microcrystalline cellulose, polysorbate 80, red iron oxide, sodium starch glycolate, titanium dioxide, and yellow iron oxide.

EPIVIR-HBV oral solution: artificial strawberry and banana flavors, citric acid (anhydrous), methylparaben, propylene glycol, propylparaben, sodium citrate (dihydrate), and sucrose (200 mg per mL).

This Patient Information has been approved by the U.S. Food and Drug Administration.

EPIVIR-HBV is a registered trademark of the GlaxoSmithKline group of companies.

EPIVIR, COMBIVIR, EPZICOM, and TRIZIVIR are registered trademarks of the ViiV Healthcare group of companies.

The other brands listed are trademarks of their respective owners and are not trademarks of the GlaxoSmithKline group of companies. The makers of these brands are not affiliated with and do not endorse the GlaxoSmithKline group of companies or its products.

GlaxoSmithKline

Research Triangle Park, NC 27709

Manufactured under agreement from

Shire Pharmaceuticals Group plc

Basingstoke, UK

©2013, GlaxoSmithKline group of companies. All rights reserved.

This Product was Repackaged By:

State of Florida DOH Central Pharmacy
104-2 Hamilton Park Drive
Tallahassee, FL 32304
USA

PACKAGE LABEL

Label Image for 53808-0893
100mg